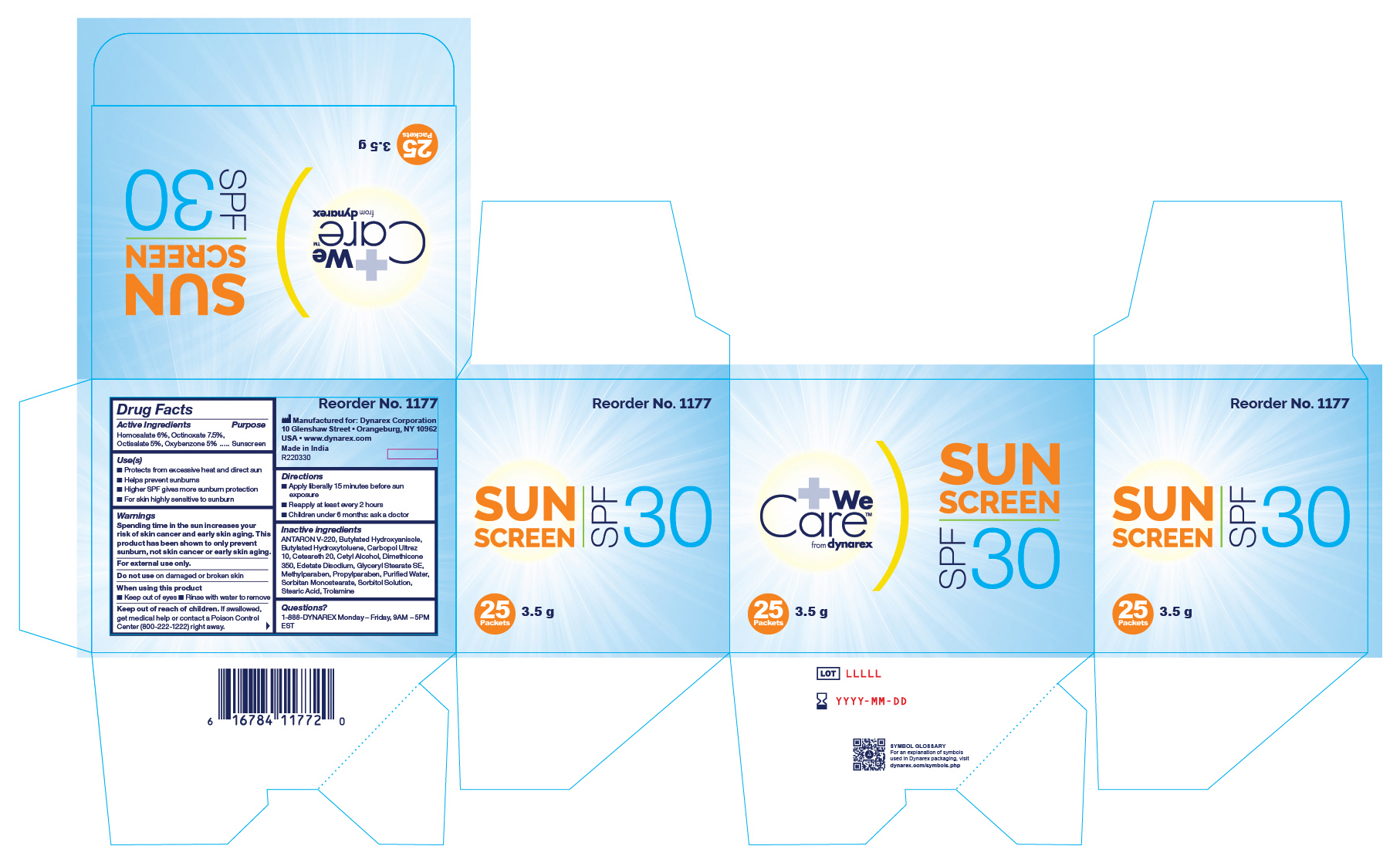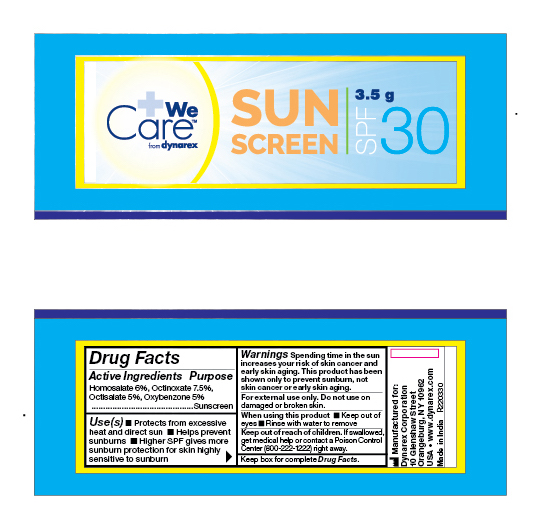 DRUG LABEL: 1177, 1178 Sunscreen
NDC: 67777-177 | Form: CREAM
Manufacturer: Dynarex
Category: otc | Type: HUMAN OTC DRUG LABEL
Date: 20241120

ACTIVE INGREDIENTS: OCTINOXATE 7.5 g/100 g; OXYBENZONE 5 g/100 g; HOMOSALATE 6 g/100 g; OCTISALATE 5 g/100 g
INACTIVE INGREDIENTS: CARBOMER INTERPOLYMER TYPE A (55000 CPS); EDETATE DISODIUM; DIMETHICONE 350; SORBITOL SOLUTION 70%; TROLAMINE; BUTYLATED HYDROXYANISOLE; EICOSYL POVIDONE; SORBITAN MONOSTEARATE; CETYL ALCOHOL; WATER; BUTYLATED HYDROXYTOLUENE; PROPYLPARABEN; STEARIC ACID; POLYOXYL 20 CETOSTEARYL ETHER; GLYCERYL STEARATE SE; METHYLPARABEN

1177, 1178 Sunscreen

Active Ingredients

Homosalate 6%, Octinoxate 7.5%, Octisalate 5%, Oxygenzone 5%

Purpose

Sunscreen

Uses

. Protects from excessive heat and direct sun

. Helps prevent sunburns

. Higher SPF gives more sunburn protection

. For skin highly sensitive to sunburn

Warnings

For External Use Only.

Spending time in the sun increases your risk of skin cancer and early skin aging. This product has been shown only to prevent sunburn, not skin carcer or early skin aging.

Do not use

On damaged or broken skin

When using this product

. Keep out of eyes

. Rinse with water to remove

Keep out of reach of children.

If swallowed, get medical help or contact a Poison Control Center 800-222-1222) right away.

Directions

. Apply liberally 15 minutes before sun exposure

. Reapply at least every 2 hours

. Children under 6 months: as a doctor

Inactive ingredients

Antaron V-220, Butylated Hydroxyanisole, Butylated Hydroxytoluene, Carbopol Ultrez 10, Ceteareth 20, Cetyl Alcohol, Dimethicone 350, Edetate Disodium, Glyceryl Stearate SE, Methylparaben, Propylparaben, Purified Water, Sorbitan Monostearate, Sorbitol Solution, Stearic Acid, Trolamine

Questions?

1-888-DYNAREX Monday - Friday, 9AM - 5PM EST

Label

1177 Sunscreen

Label

1177, 1178 Sunscreen